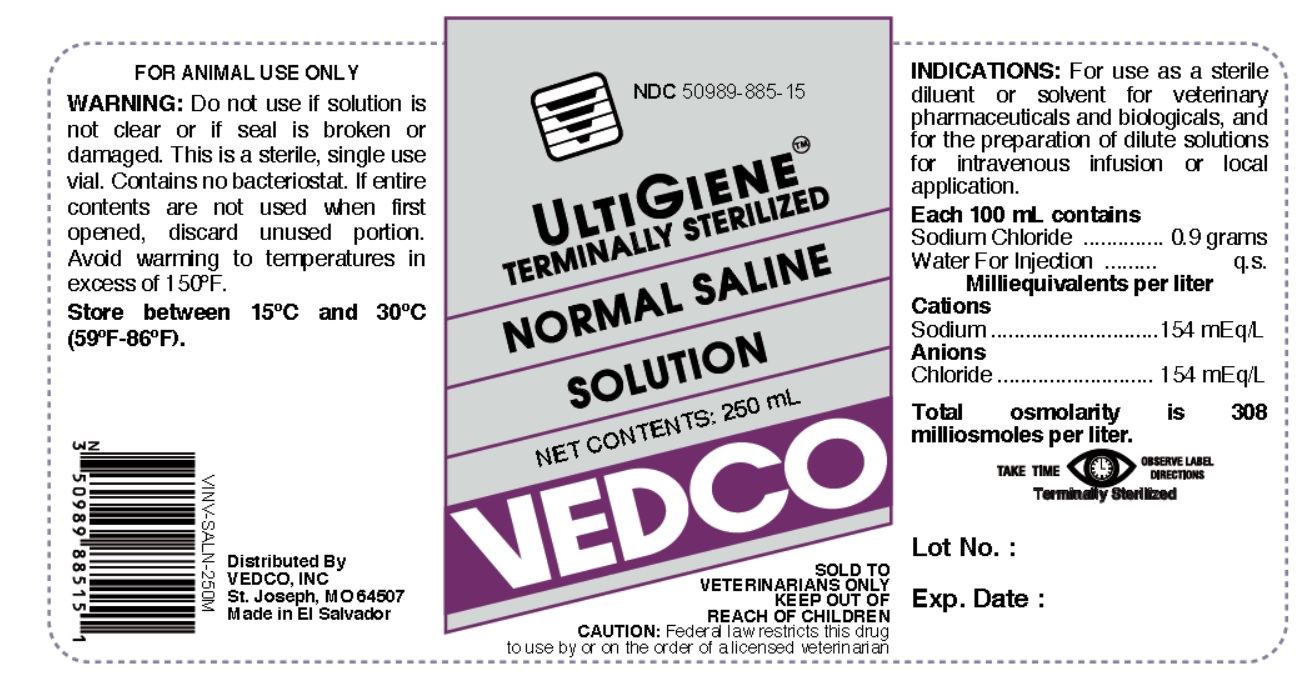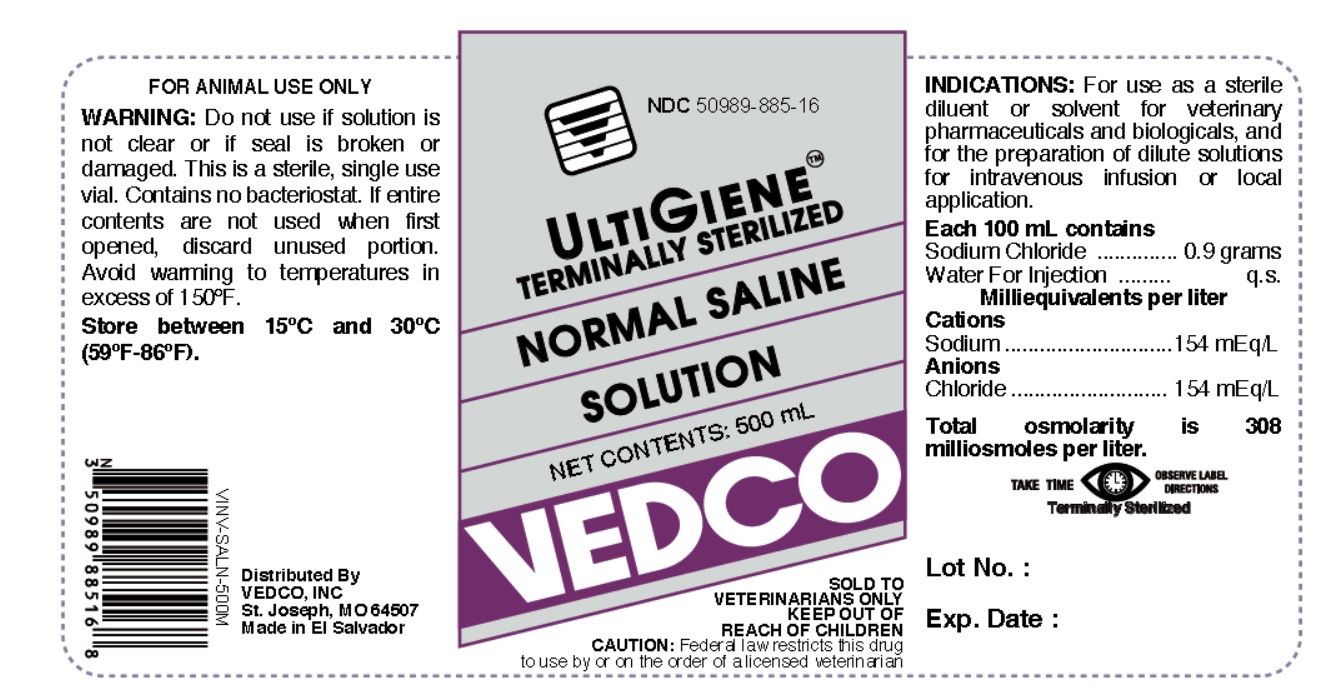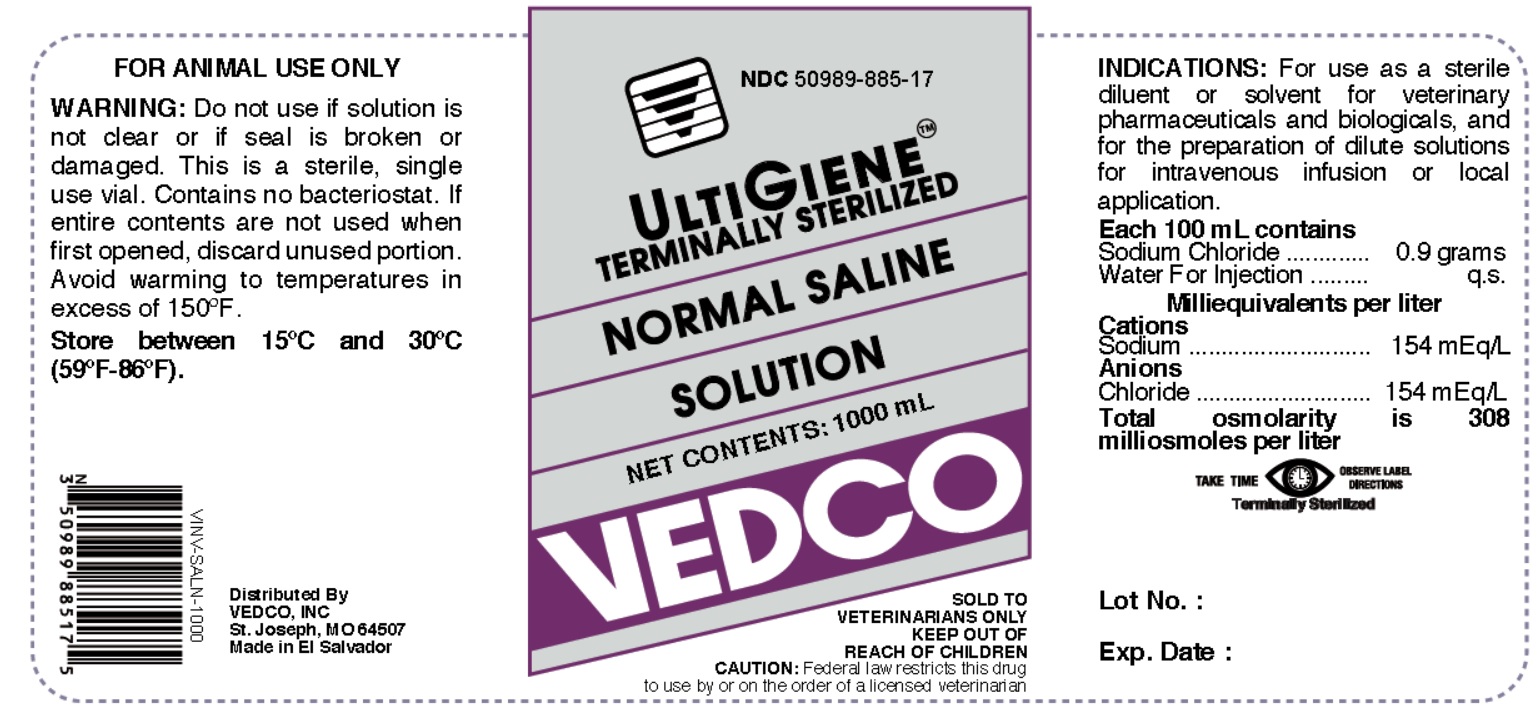 DRUG LABEL: Sterile Saline
NDC: 50989-885 | Form: INJECTION, SOLUTION
Manufacturer: Vedco
Category: animal | Type: PRESCRIPTION ANIMAL DRUG LABEL
Date: 20190312

ACTIVE INGREDIENTS: SODIUM CHLORIDE 0.9 g/100 mL

STERILE SALINE- sterile saline injection, solution

Vedco

Disclaimer: This drug has not been found by FDA to be safe and effective, and this labeling has not been approved by FDA.

NORMAL SALINE SOLUTION

FOR ANIMAL USE ONLY

SOLD TO VETERINARIANS ONLY

Active Ingredient

Each 100 mL contains:
Sodium Chloride ....... 0.9 grams
Water For Injection .............q.s.

Milliequivalents per liter

Cations
Sodium .................... 154 mEq/L

Anions
Chloride ................... 154 mEq/L

Total osmolarity is 308 milliosmoles per liter

WARNING:

Do not use if solution is not clear or if seal is broken or damaged.

This is a sterile, single use vial. Contains no bacteriostat.

If entire contents are not used whenfirst opened, discard unused portion. Avoid warming to temperatures in excess of 150°F.

STORAGE

Store between 15°C and 30°C (59°F-86°F).

KEEP OUT OF REACH OF CHILDREN

CAUTION:

Federal law restricts this drug to use by or on the order of a licensed veterinarian.

INDICATIONS:

For use as a sterile diluent or solvent for veterinary pharmaceuticals and biologicals, and for the preparation of dilute solutions for intravenous infusion or local application.

DOSAGE

TAKE TIME OBSERVE LABEL DIRECTIONS

INFORMATION FOR OWNERS/CAREGIVERS

Distributed By

VEDCO, INC.

St. Joseph, MO 64507
Made in El Salvador

STERILE SOLUTION

TABLE
CONTENT | NDC | VINV #
250 mL | 50989-885-15 | VINV-SALN-250M
500 mL | 50989-885-16 | VINV-SALN-500M
1000 mL | 50989-885-17 | VINV-SALN-1000

PRINCIPAL DISPLAY PANEL

NDC 50989-885-15

ULTIGIENE TERMINALLY STERILIZED

NORMAL SALINE SOLUTION

NET CONTENTS: 250 mL

VEDCO

SOLD TO VETERINARIANS ONLY

KEEP OUT OF REACH OF CHILDREN

CAUTION: Federal Law (U.S.A) restricts this drug to use by or on the order of a licensed veterinarian

NDC 50989-885-16

ULTIGIENE TERMINALLY STERILIZED

NORMAL SALINE SOLUTION

NET CONTENTS: 500 mL

VEDCO

SOLD TO VETERINARIANS ONLY

KEEP OUT OF REACH OF CHILDREN

CAUTION: Federal Law (U.S.A) restricts this drug to use by or on the order of a licensed veterinarian

NDC 50989-885-17

ULTIGIENE TERMINALLY STERILIZED

NORMAL SALINE SOLUTION

NET CONTENTS: 1000 mL

VEDCO

SOLD TO VETERINARIANS ONLY

KEEP OUT OF REACH OF CHILDREN

CAUTION: Federal Law (U.S.A) restricts this drug to use by or on the order of a licensed veterinarian